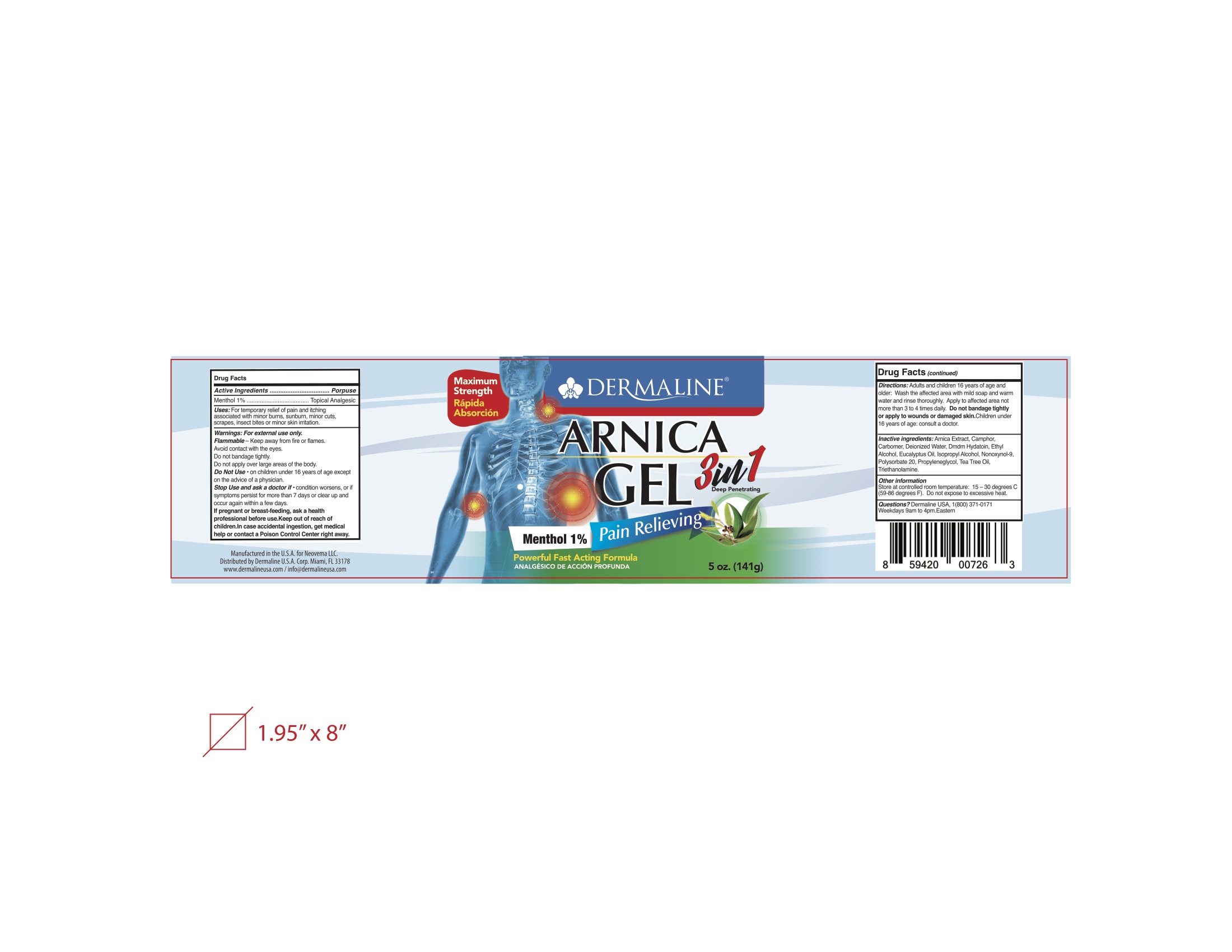 DRUG LABEL: Topical Analgesic
NDC: 82165-104 | Form: GEL
Manufacturer: Dermaline USA Corp
Category: otc | Type: HUMAN OTC DRUG LABEL
Date: 20230214

ACTIVE INGREDIENTS: MENTHOL 1 g/100 g
INACTIVE INGREDIENTS: ALCOHOL; EUCALYPTUS OIL; POLYSORBATE 20; WATER; ISOPROPYL ALCOHOL; AMMONIUM NONOXYNOL-9 SULFATE; 2-PHENYLPROPANAL PROPYLENE GLYCOL ACETAL; DMDM HYDANTOIN; TEA TREE OIL; CUPRIC TRIETHANOLAMINE; CAMPHOR (SYNTHETIC); CARBOMER 940; ARNICA MONTANA

Dermaline Arnica Gel

Active Ingredient(s)

Menthol 1%. Purpose: Topical Analgesic

Purpose

Topical Analgesic, Gel

Use

For temporary relief of pain and itching associated with minor burns, sunburn, minor cuts, scrapes, insect bites or minor skin irritation.

Warnings

For external use only. Flammable. Keep away from fire or flames.

Avoid Contact with eyes. Do not bandage tightly.

Do not apply over large areas of the body.

Do not use

- on children under 16 years of age except on the advice of a physician.

When using this product keep out of eyes, ears, and mouth. In case of contact with eyes, rinse eyes thoroughly with water.
Stop use and ask a doctor if irritation or rash occurs. These may be signs of a serious condition.
Keep out of reach of children. If swallowed, get medical help or contact a Poison Control Center right away.

Stop use and ask a doctor if condition worsens, or if symptoms persist for more than 7 days or clear up and occur again within a few days.

If pregnant or breast-feeding, ask a health professional before use.

Keep out of reach of children.

Incase accidental ingestion, get medical help or contact a Poison Control Center right away.

Keep out of reach of children. If swallowed, get medical help or contact a Poison Control Center right away.

Directions

Adults and children 16 years of age and older: Wash the affected area with mild soap and warm

water and rinse thoroughly. Apply to affected area not more than 3 to 4 times daily.

Do not bandage tightly or apply to wounds or damaged skin.

Children under 16 yeats of age: consult a doctor.

Other information

- Store between 15-30C (59-86F)
- Do not expose to excessive heat.

Inactive ingredients

Arnica Extract, Camphor, Carbomer, Deionized Water, DMDM Hydatoin, Ethyl Alcohol, Eucalyptus Oil, Isopropyl Alcohol, Nonoxynol-9, polysorbate 20, propyleneglycol, Tea Tree Oil, Trirthanolamine.

Package Label - Principal Display Panel

141 g